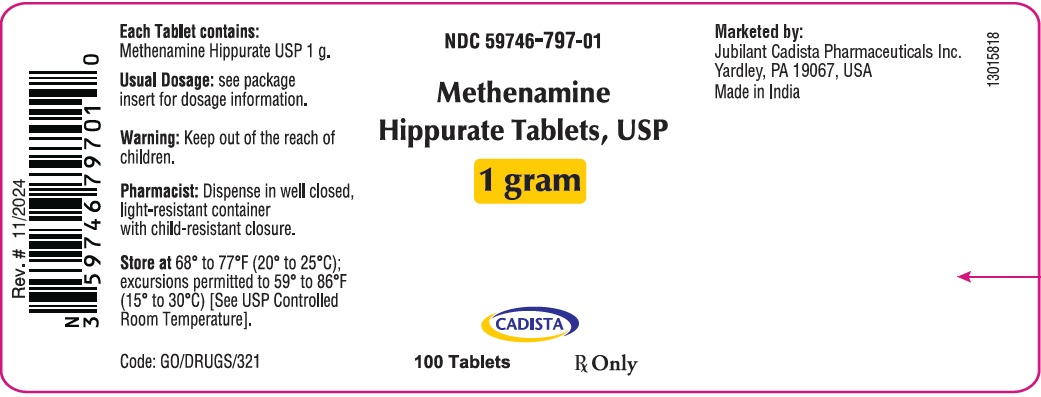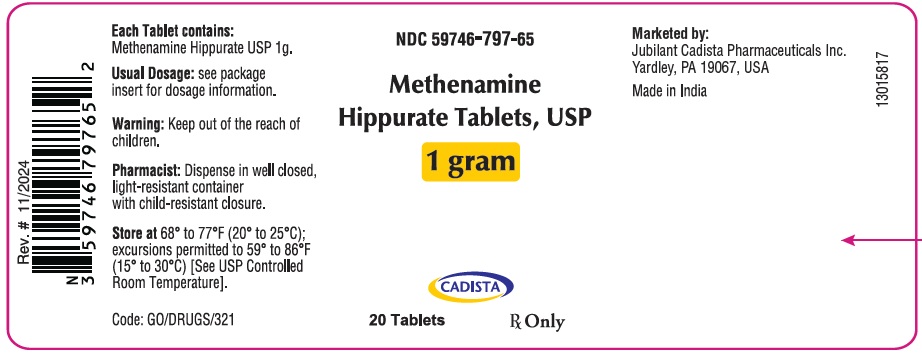 DRUG LABEL: Methenamine Hippurate
NDC: 59746-797 | Form: TABLET
Manufacturer: Jubilant Cadista Pharmaceuticals Inc.
Category: prescription | Type: Human Prescription Drug Label
Date: 20260203

ACTIVE INGREDIENTS: METHENAMINE HIPPURATE 1 g/1 1
INACTIVE INGREDIENTS: Silicon Dioxide; Microcrystalline Cellulose; Magnesium Stearate; Povidone, Unspecified; Sodium Starch Glycolate Type A

Methenamine Hippurate Tablets, USP

To reduce the development of drug-resistant bacteria and maintain the effectiveness of methenamine hippurate tablets and other antibacterial drugs, methenamine hippurate should be used only to treat or prevent infections that are proven or strongly suspected to be caused by bacteria.

DESCRIPTION

Each white to off-white capsule shaped tablet contains 1g Methenamine Hippurate, USP which is the Hippuric Acid Salt of Methenamine (hexamethylene tetramine). The tablet also contains inactive ingredients colloidal silicon dioxide, microcrystalline cellulose, magnesium stearate, povidone and sodium starch glycolate.

ACTIONS

Microbiology: Methenamine hippurate tablets has antibacterial activity because the methenamine component is hydrolyzed to formaldehyde in acid urine. Hippuric acid, the other component, has some antibacterial activity and also acts to keep the urine acid. The drug is generally active against E. coli, enterococci and staphylococci. Enterobacter aerogenes is generally resistant. The urine must be kept sufficiently acid for urea-splitting organisms such as Proteus and Pseudomonas to be inhibited.

Susceptibility Testing:
For specific information regarding susceptibility test interpretive criteria and associated test methods and quality control standards recognized by FDA for this drug, please see: https://www.fda.gov/STIC.

Human Pharmacology: Within 1/2 hour after ingestion of a single 1-gram dose of methenamine hippurate, antibacterial activity is demonstrable in the urine. Urine has continuous antibacterial activity when methenamine hippurate is administered at the recommended dosage schedule of 1 gram twice daily. Over 90% of methenamine moiety is excreted in the urine within 24 hours after administration of a single 1gram dose. Similarly, the hippurate moiety is rapidly absorbed and excreted, and it reaches the urine by both tubular secretion and glomerular filtration. This action may be important in older patients or in those with some degree of renal impairment.

INDICATIONS

Methenamine hippurate tablets, USP is indicated for prophylactic or suppressive treatment of frequently recurring urinary tract infections when long-term therapy is considered necessary. This drug should only be used after eradication of the infection by other appropriate antimicrobial agents.

To reduce the development of drug-resistant bacteria and maintain the effectiveness of methenamine hippurate tablets, USP and other antibacterial drugs, methenamine hippurate tablets, USP should be used only to treat or prevent infections that are proven or strongly suspected to be caused by susceptible bacteria. When culture and susceptibility information are available, they should be considered in selecting or modifying antibacterial therapy. In the absence of such data, local epidemiology and susceptibility patterns may contribute to the empiric selection of therapy.

CONTRAINDICATIONS

Methenamine hippurate tablets are contraindicated in patients with renal insufficiency, severe hepatic insufficiency, or severe dehydration. Methenamine preparations should not be given to patients taking sulfonamides because some sulfonamides may form an insoluble precipitate with formaldehyde in the urine.

WARNING

Large doses of methenamine (8 grams daily for 3 to 4 weeks) have caused bladder irritation, painful and frequent micturition, albuminuria, and gross hematuria.

PRECAUTIONS

Geriatric Use

Clinical studies of methenamine hippurate tablets did not include sufficient numbers of subjects aged 65 and over to determine whether they respond differently from younger subjects. Other reported clinical experience has not identified differences in responses between the elderly and younger patients. In general, dose selection for an elderly patient should be cautious, usually starting at the low end of the dosing range, reflecting the greater frequency of decreased hepatic, renal or cardiac function, and of concomitant disease or other drug therapy.

Methenamine hippurate tablets, USP are contraindicated in patients with renal insufficiency and severe hepatic insufficiency (see CONTRAINDICATIONS).

Information for Patients

Patients should be counseled that antibacterial drugs including methenamine hippurate tablets should only be used to treat bacterial infections. They do not treat viral infections (e.g., the common cold). When methenamine hippurate tablets is prescribed to treat a bacterial infection, patients should be told that although it is common to feel better early in the course of therapy, the medication should be taken exactly as directed. Skipping doses or not completing the full course of therapy may (1) decrease the effectiveness of the immediate treatment and (2) increase the likelihood that bacteria will develop resistance and will not be treatable by methenamine hippurate tablets or other antibacterial drugs in the future.

ADVERSE REACTIONS

Minor adverse reactions have been reported in less than 3.5% of patients treated. These reactions have included nausea, upset stomach, dysuria, and rash.

To report SUSPECTED ADVERSE REACTIONS, contact Jubilant Cadista Pharmaceuticals Inc. at 1-800-313-4623 or FDA at 1-800-FDA-1088 or www.fda.gov/medwatch.

DOSAGE AND ADMINISTRATION

1 tablet (1.0 g) twice daily (morning and night) for adults and pediatric patients over 12 years of age. 1/2 to 1 tablet (0.5 to 1 g) twice daily (morning and night) for pediatric patients 6 to 12 years of age. Since the antibacterial activity of methenamine hippurate tablets, USP is greater in acid urine, restriction of alkalinizing foods and medications is desirable. If necessary, as indicated by urinary pH and clinical response, supplemental acidification of the urine should be instituted. The efficacy of therapy should be monitored by repeated urine cultures.

HOW SUPPLIED

Methenamine Hippurate Tablets USP, 1 g are white to off-white capsule shaped tablet, debossed with “L” and “59” on one side and break line (functional) on other side.

Bottle pack of 20 tablets with Child Resistant Closure, NDC 59746-797-65
Bottle pack of 100 tablets with Child Resistant Closure, NDC 59746-797-01

Store at 68° to 77°F (20° to 25°C); excursions permitted to 59° to 86°F (15° to 30°C) [See USP Controlled Room Temperature].
Dispense in well-closed, light-resistant container with child-resistant closure.

Rx Only
Marketed by:
Jubilant Cadista Pharmaceuticals Inc.
Yardley, PA 19067, USA
Revision 01/2026

PRINCIPAL DISPLAY PANEL

NDC 59746-797-65
Methenamine
Hippurate Tablets, USP
1 gram
CADISTA
20 Tablets
Rx Only
Each Tablet contains:
Methenamine Hippurate USP 1g.
Usual Dosage: see package
insert for dosage information.
Warning: Keep out of the reach of
children.
Pharmacist: Dispense in well closed,
light-resistant container
with child-resistant closure.
Store at 68° to 77°F (20° to 25°C);
excursions permitted to 59° to 86°F
(15° to 30°C) [See USP Controlled
Room Temperature].
Code: G0/DRUGS/321
Marketed by:
Jubilant Cadista Pharmaceuticals Inc.
Yardley, PA 19067, USA
Made in India
13015817

NDC 59746-797-01
Methenamine
Hippurate Tablets, USP
1 gram
CADISTA
100 Tablets
Rx Only
Each Tablet contains:
Methenamine Hippurate USP 1g.
Usual Dosage: see package
insert for dosage information.
Warning: Keep out of the reach of
children.
Pharmacist: Dispense in well closed,
light-resistant container
with child-resistant closure.
Store at 68° to 77°F (20° to 25°C);
excursions permitted to 59° to 86°F
(15° to 30°C) [See USP Controlled
Room Temperature].
Code: G0/DRUGS/321
Marketed by:
Jubilant Cadista Pharmaceuticals Inc.
Yardley, PA 19067, USA
Made in India
13015818